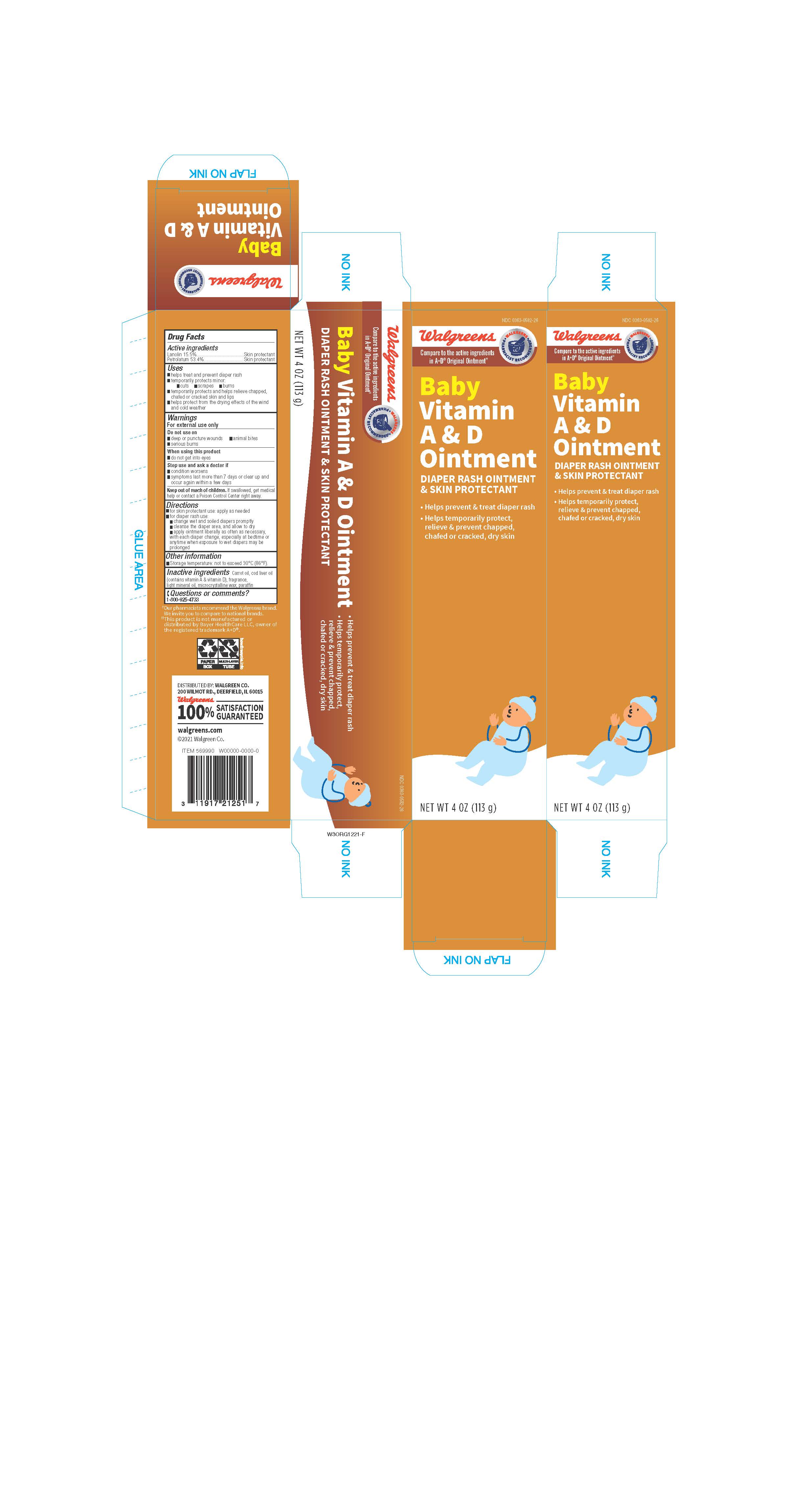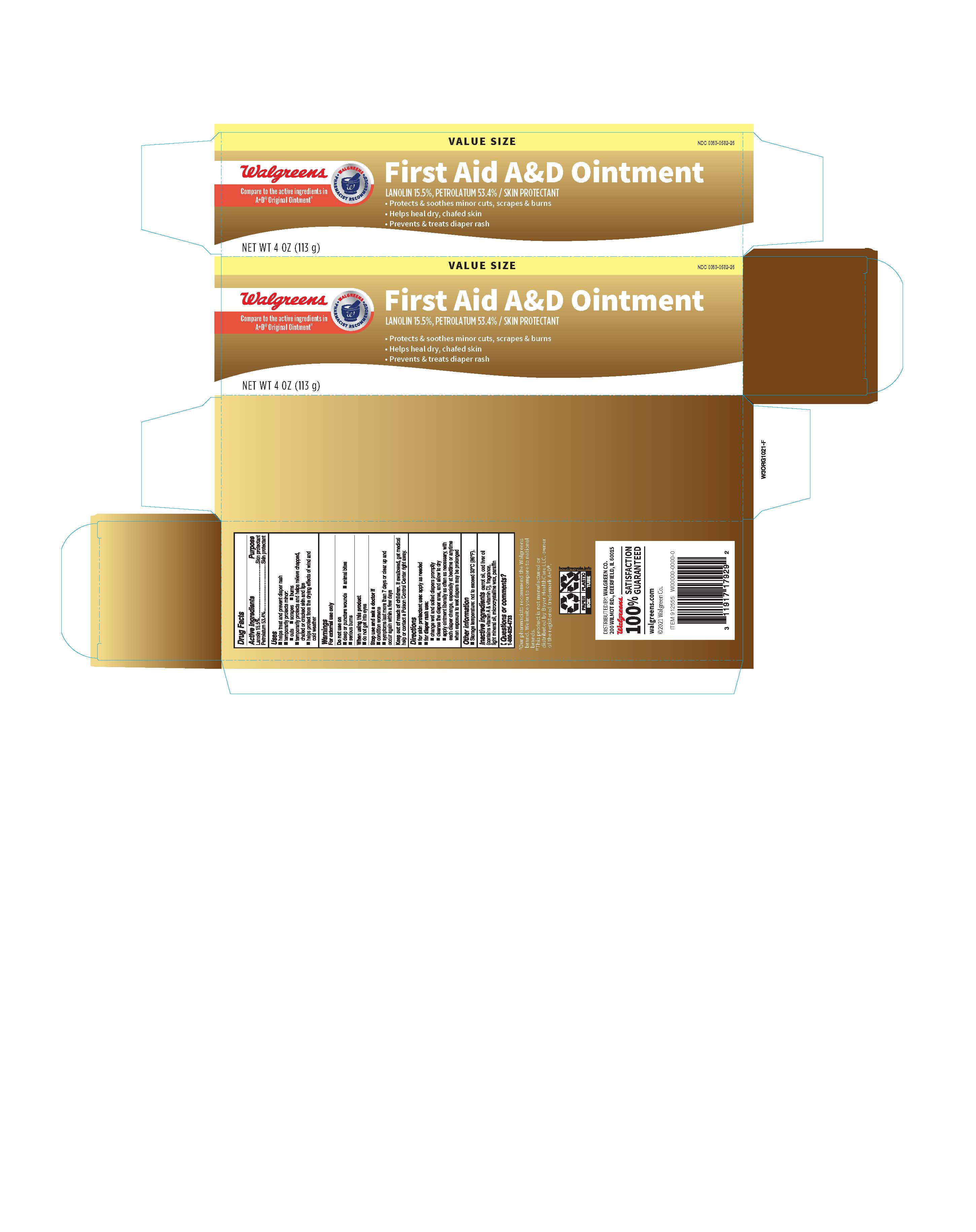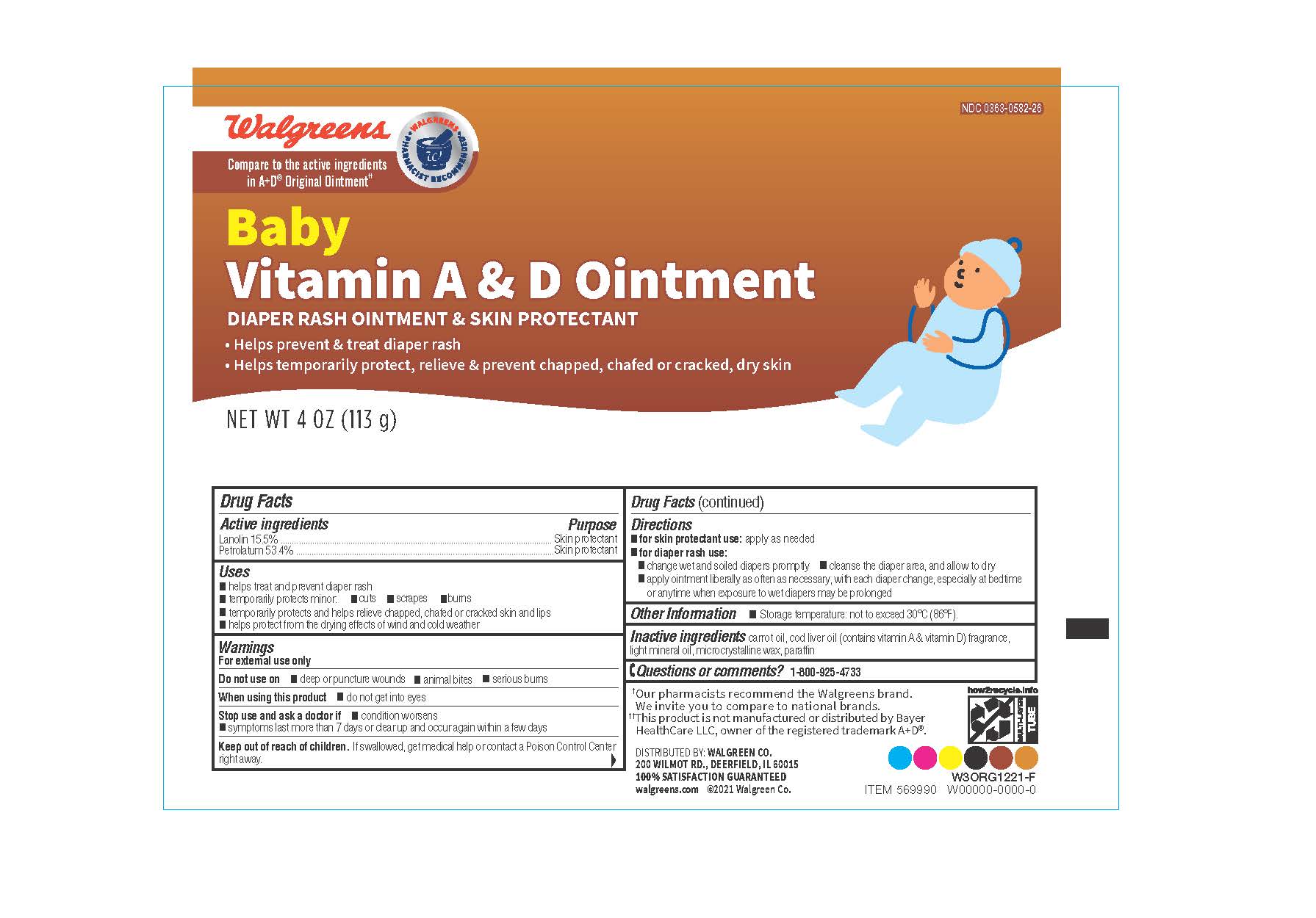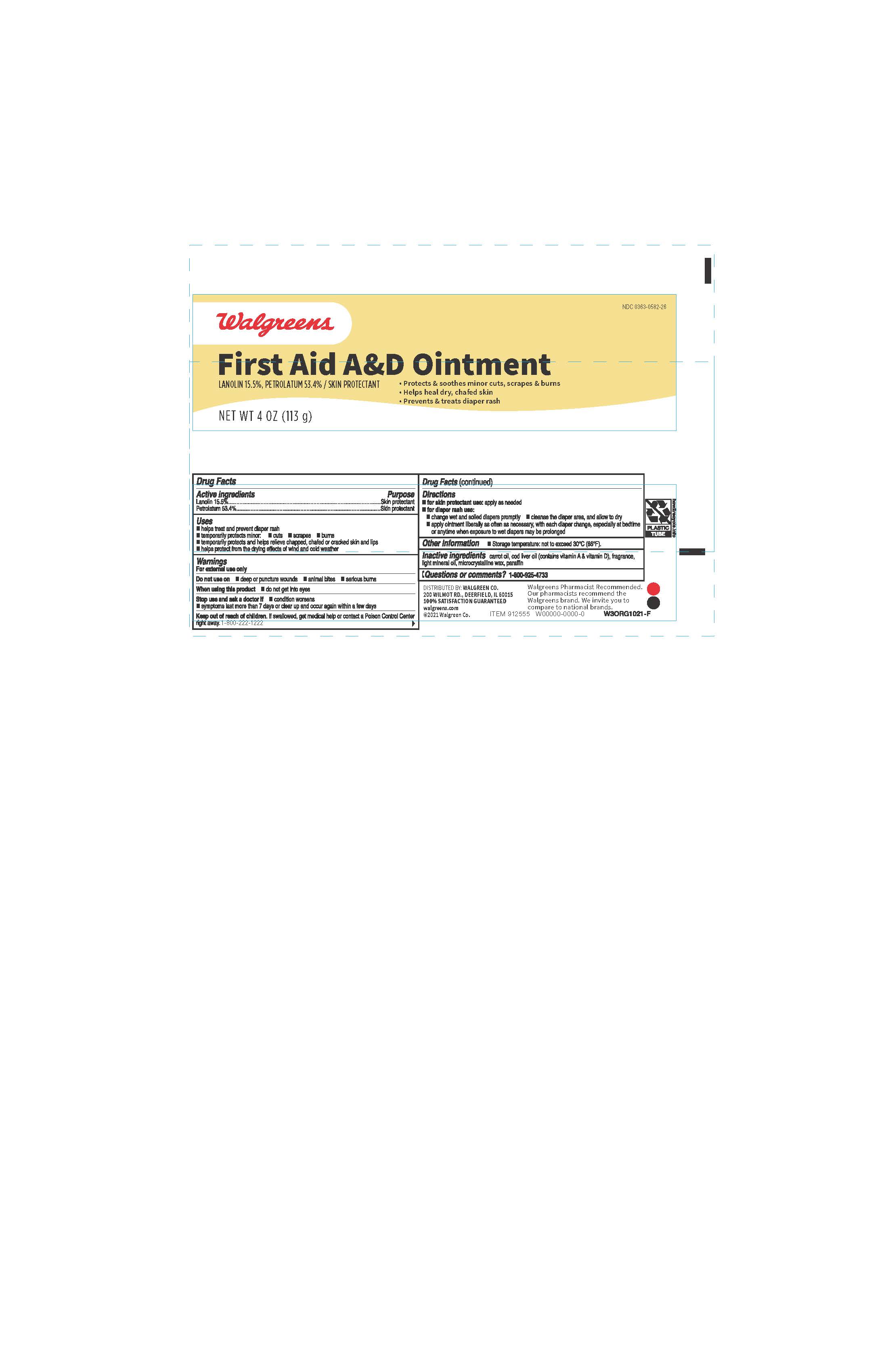 DRUG LABEL: Walgreens Vitamin A and D
NDC: 0363-0582 | Form: OINTMENT
Manufacturer: Walgreen Company
Category: otc | Type: HUMAN OTC DRUG LABEL
Date: 20260115

ACTIVE INGREDIENTS: PETROLATUM 53.4 g/100 g; LANOLIN 15.5 g/100 g
INACTIVE INGREDIENTS: MICROCRYSTALLINE WAX; PARAFFIN; LIGHT MINERAL OIL; COD LIVER OIL; CARROT SEED OIL; VITAMIN A; VITAMIN D

Walgreen Vitamin A & D Ointment and Baby Vitamin A&D

Active ingredients

Lanolin 15.5%

Petrolatum 53.4%

Purpose

Diaper rash ointment

Skin protectant

Uses

- helps treat and prevent diaper rash
- temporarily protects minor:
- cuts
- scrapes
- burns
- temporarily protects and helps relieve chapped, chafed or cracked skin and lips
- protects chafed skin due to diaper rash and helps seal out wetness

Warnings

For external use only

Do not use on

- deep or puncture wounds
- animal bites
- serious burns

When using this product

- do not get into eyes

Stop use and ask a doctor if

- condition worsens
- symptoms last more than 7 days or clear up and occur again within a few days

Keep out of reach of children.

If swallowed, get medical help or contact a Poison Control Center right away (1-800-222-1222).

Directions

- for skin protectant use: apply as needed
- for diaper rash use:
- change wet and soiled diapers promptly
- cleanse the diaper area, and allow to dry
- apply ointment liberally as often as necessary, with each diaper change, especially at bedtime or anytime when exposure to wet diapers may be prolonged

Other information

- store at 20°-25°C (68°-77°F)

Inactive ingredients

carrot oil, cod liver oil (contains vitamin A & vitamin D), fragrance, light mineral oil, microcrystalline wax, paraffin

Questions or comments?

1-800-719-9260